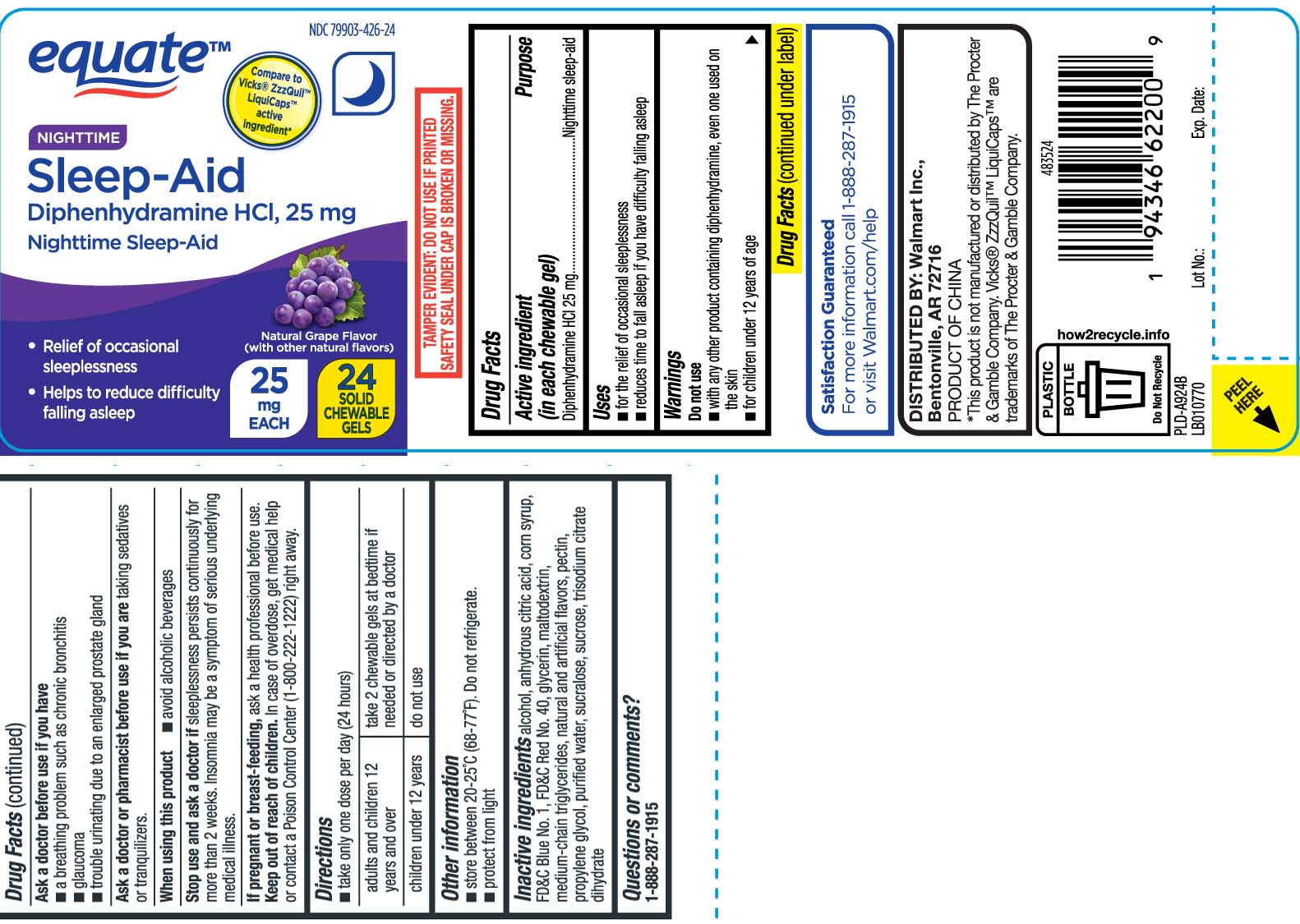 DRUG LABEL: Sleep-Aid
NDC: 79903-426 | Form: CHEWABLE GEL
Manufacturer: WALMART INC. (see also Equate)
Category: otc | Type: HUMAN OTC DRUG LABEL
Date: 20260213

ACTIVE INGREDIENTS: DIPHENHYDRAMINE HYDROCHLORIDE 25 mg/1 1
INACTIVE INGREDIENTS: ALCOHOL; ANHYDROUS CITRIC ACID; CORN SYRUP; PECTIN; WATER; TRISODIUM CITRATE DIHYDRATE; SUCRALOSE; SUCROSE; FD&C BLUE NO. 1; FD&C RED NO. 40; GLYCERIN; MALTODEXTRIN; MEDIUM-CHAIN TRIGLYCERIDES; PROPYLENE GLYCOL

Drug Facts

Active ingredient (in each chewable gel)

Diphenhydramine HCl 25 mg

Purpose

Nighttime sleep-aid

Uses

- For the relief of occasional sleeplessness
- reduce time to fall asleep if you have difficulty falling asleep

Warnings

Do not use

- with any other product containing diphenhydramine, even one used on skin
- for children under 12 years of age

Ask a doctor before use if you have

- a breathing problem such as chronic bronchitis
- glaucoma
- trouble urinating due to an enlarged prostate gland

Ask a doctor or pharmacist before use if you are

taking sedatives or tranquilizers.

When using this product

- avoid alcoholic beverages

Stop use and ask a doctor if

sleeplessness persists continuously for more than 2 weeks. Insomnia may be a symptom of serious underlying medical illness

If pregnant of breast-feeding,

ask a health professional before use.

Keep out of reach of children.

In case of overdose, get medical help or contact a Poison Control Center (1-800-222-1222) right away.

Directions

- take only one chewable gel per day (24 hours)

adults and children 12 years and over | take 2 chewable gel at bedtime if needed or directed by a doctor
children under 12 years | do not use

Other information

- store between 20-25ºC (68° to 77°F). Do not refrigerate
- protect from light

Inactive ingredients

Alcohol, anhydrous citric acid, corn syrup, FD&C blue #1, FD&C red #40, glycerin, maltodextrin, medium-chain triglycerides, natural and artifical flavors, pectin, propylene glycol, purified water, sucralose, sucrose, trisodium citrate dihydrate

Questions or comments?

Call 1-888-287-1915

Principal Display Panel

*Compare to Vicks® ZzzQuil™ LiquiCaps™ active ingredient*

NIGHTTIME

Sleep-Aid

Diphenhydramine HCl 25 mg

Nighjttime sleep-aid

- Relief of occasional sleeplessness
- Helps to reduce difficulty falling asleep

*This product is not manufactured or distributed by The Procter & Gamble Company. Vicks® ZzzQuil™ LiquiCaps™ are trademarks of The Procter & Gamble Company.

TAMPER EVIDENT: DO NOT USE IF PRINTED SAFETY SEAL UNDER CAP IS BROKEN OR MISSING

DISTRIBUTED BY: Walmart Inc.,

Bentonville, AR 72716

Product Label

EQUATE Nighttime Sleep-Aid